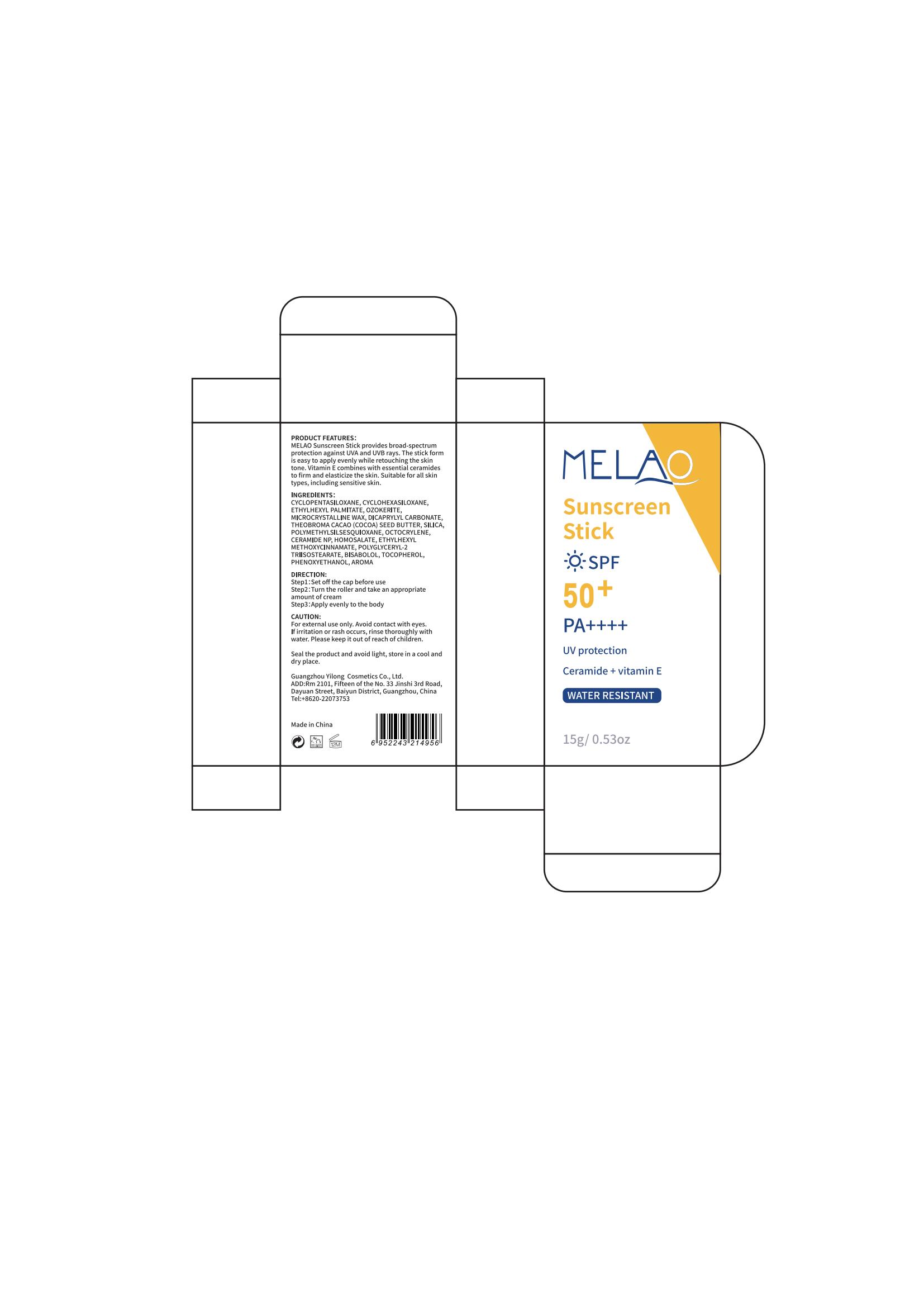 DRUG LABEL: MELAO Sunscreen Stick
NDC: 83566-188 | Form: STICK
Manufacturer: Guangdong Aimu Biological Technology Co., Ltd
Category: otc | Type: HUMAN OTC DRUG LABEL
Date: 20250625

ACTIVE INGREDIENTS: CERAMIDE NP 2 g/100 g; TOCOPHEROL 2 g/100 g; OCTOCRYLENE 5 g/100 g
INACTIVE INGREDIENTS: ETHYLHEXYL PALMITATE; POLYGLYCERYL-2 TRIISOSTEARATE

MELAO Sunscreen Stick

Active ingredients

Active ingredients 5%

CERAMIDE NP 2%

TOCOPHEROL 2%

Purpose

sunscreen

Uses

Step1：Set off the cap before use
Step2：Turn the roller and take an appropriate amount of cream
Step3：Apply evenly to the body

Warnings

For external use only.

Stop use and ask a doctor if

rash occurs.

Do not use

on damaged or broken skin.

When using this product

keep out of eyes. Rinse with water to remove.

Keep out of reach of children.

If swallowed, get medical help or contact a Poison Control Center right away.

Dosage

Turn the roller and take an appropriate amount of cream
Apply evenly to the body

Inactive ingredients

CYCLOPENTASILOXANE, CYCLOHEXASILOXANE, ETHYLHEXYL PALMITATE, OZOKERITE, MICROCRYSTALLINE WAX, DICAPRYLYL CARBONATE, THEOBROMA CACAO (COCOA) SEED BUTTER, SILICA, POLYMETHYLSILSESQUIOXANE, HOMOSALATE, ETHYLHEXYL METHOXYCINNAMATE, POLYGLYCERYL-2 TRIISOSTEARATE, BISABOLOL, PHENOXYETHANOL, AROMA